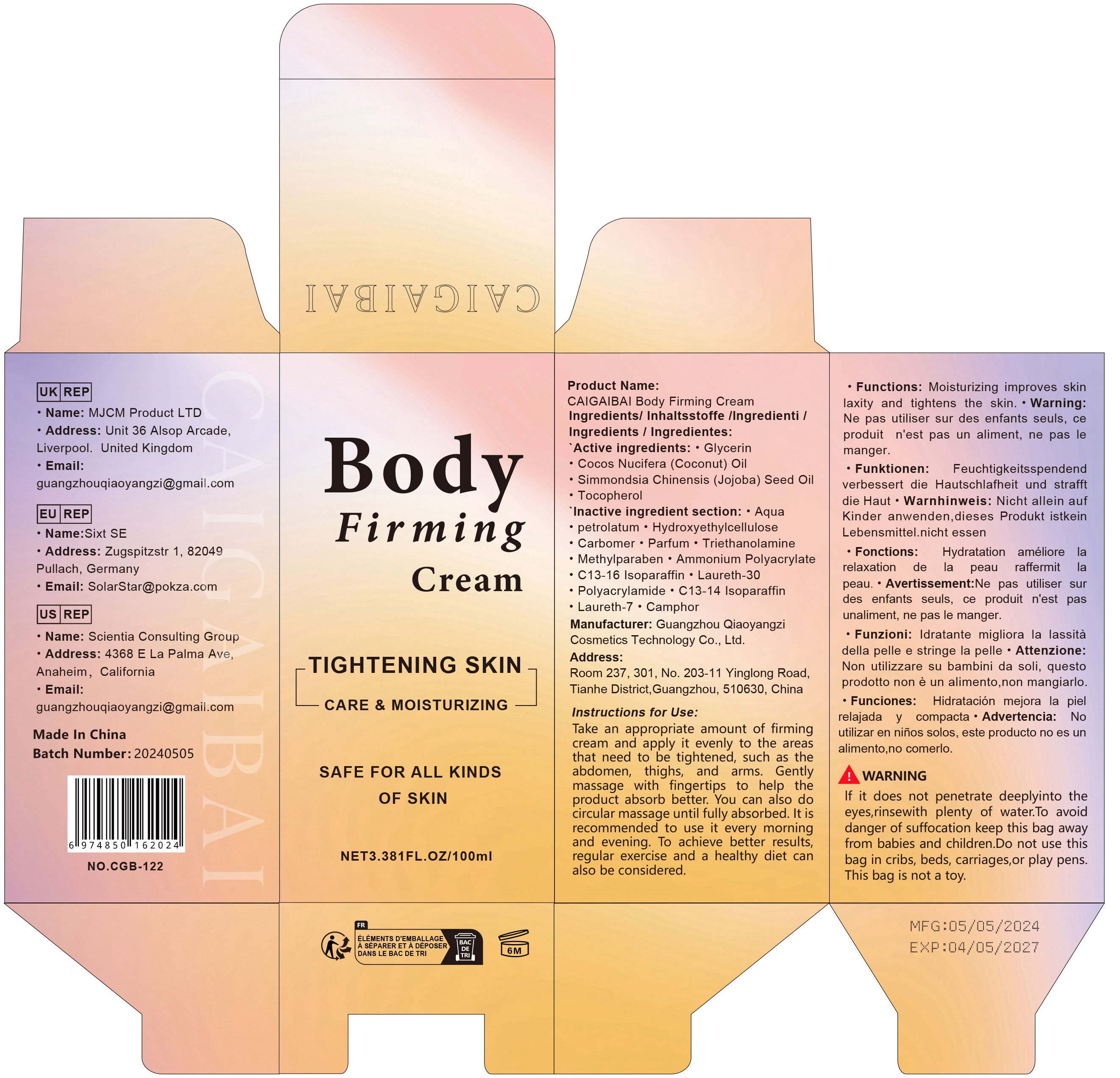 DRUG LABEL: Body Firming Cream
NDC: 84751-122 | Form: EMULSION
Manufacturer: Guangzhou Qiaoyangzi Cosmetics Technology Co Ltd
Category: otc | Type: HUMAN OTC DRUG LABEL
Date: 20241024

ACTIVE INGREDIENTS: TOCOPHEROL 0.1 mg/100 mg; JOJOBA OIL 0.1 mg/100 mg; COCONUT OIL 0.1 mg/100 mg; GLYCERIN 8.9 mg/100 mg
INACTIVE INGREDIENTS: PARFUMIDINE 0.5 mg/100 mg; TRIETHANOLAMINE 0.5 mg/100 mg; CARBOMER 0.8 mg/100 mg; PETROLATUM 10 mg/100 mg; METHYLPARABEN 0.1 mg/100 mg; AQUA 76.9 mg/100 mg; HYDROXYETHYL CELLULOSE, UNSPECIFIED 1 mg/100 mg

Active ingredients

Glycerin 8.90%
Cocos Nucifera (Coconut) Oil 0.10%
Simmondsia Chinensis (Jojoba) Seed Oil 0.10%
Tocopherol 0.10%

INACTIVE INGREDIENT SECTION

Aqua 76.90%
Petrolatum 10.00%
Hydroxyethylcellulose 1.00%
Carbomer 0.80%
Parfum 0.50%
Triethanolamine 0.50%
Methylparaben 0.10%
Ammonium Polyacrylate 0.25%
C13-16 Isoparaffin 0.20%
Laureth-30 0.15%
Polyacrylamide 0.10%
C13-14 Isoparaffin 0.10%
Laureth-7 0.10%
Camphor 0.10%

Purpose

Enhancing Skin Elasticity: Helps improve skin firmness and elasticity, reducing sagging.
Moisturizing and Hydrating: Provides deep hydration to keep the skin soft and smooth.
Improving Skin Texture: Helps to smooth the skin's surface, reducing roughness and fine lines.
Sculpting the Body: Makes the skin appear more toned.

Uses

Dispense an appropriate amount of firming cream and apply it evenly to the areas that need tightening, such as the abdomen, thighs, and arms. Gently massage the applied areas with your fingertips to help the product absorb better. You can use circular motions to massage until the cream is fully absorbed. It is recommended to use daily, both morning and evening. For better results, you can also incorporate regular exercise and a healthy diet.

Warnings

Do not enter the eyes when using. Rinse with plenty ofwater and keep out of reach of children. Not edible

Stop use

Discontinue use and consult a physician if any skin irritation, redness, itching, or allergic reaction occurs.

Do not use

If you are allergic to any of the ingredients.
On broken, inflamed, or irritated skin.
In conjunction with other hair loss treatments.

Keep out of reach of children!

To avoid danger of suffocation, keep this bag away from babies and children. Do not use this bag in cribs, beds, carriages, or play pens. This bag is not a toy.

Precautions for Use

lf it does not penetrate deeplyinto the eyes, rinse
with plenty of water.Do not use on children alone, this product is not food,
do not eat.

Instructions for Use

Dispense an appropriate amount of firming cream and apply it evenly to the areas that need tightening, such as the abdomen, thighs, and arms. Gently massage the applied areas with your fingertips to help the product absorb better. You can use circular motions to massage until the cream is fully absorbed. It is recommended to use daily, both morning and evening. For better results, you can also incorporate regular exercise and a healthy diet.

DOSAGE & ADMINISTRATION SECTION

DOSAGE & ADMINISTRATION:
Use approximately one to two pumps of oil per application.
Apply evenly to dry scalp and hair, gently massaging to enhance absorption.
Frequency can be adjusted as needed, but daily use is recommended for best results.